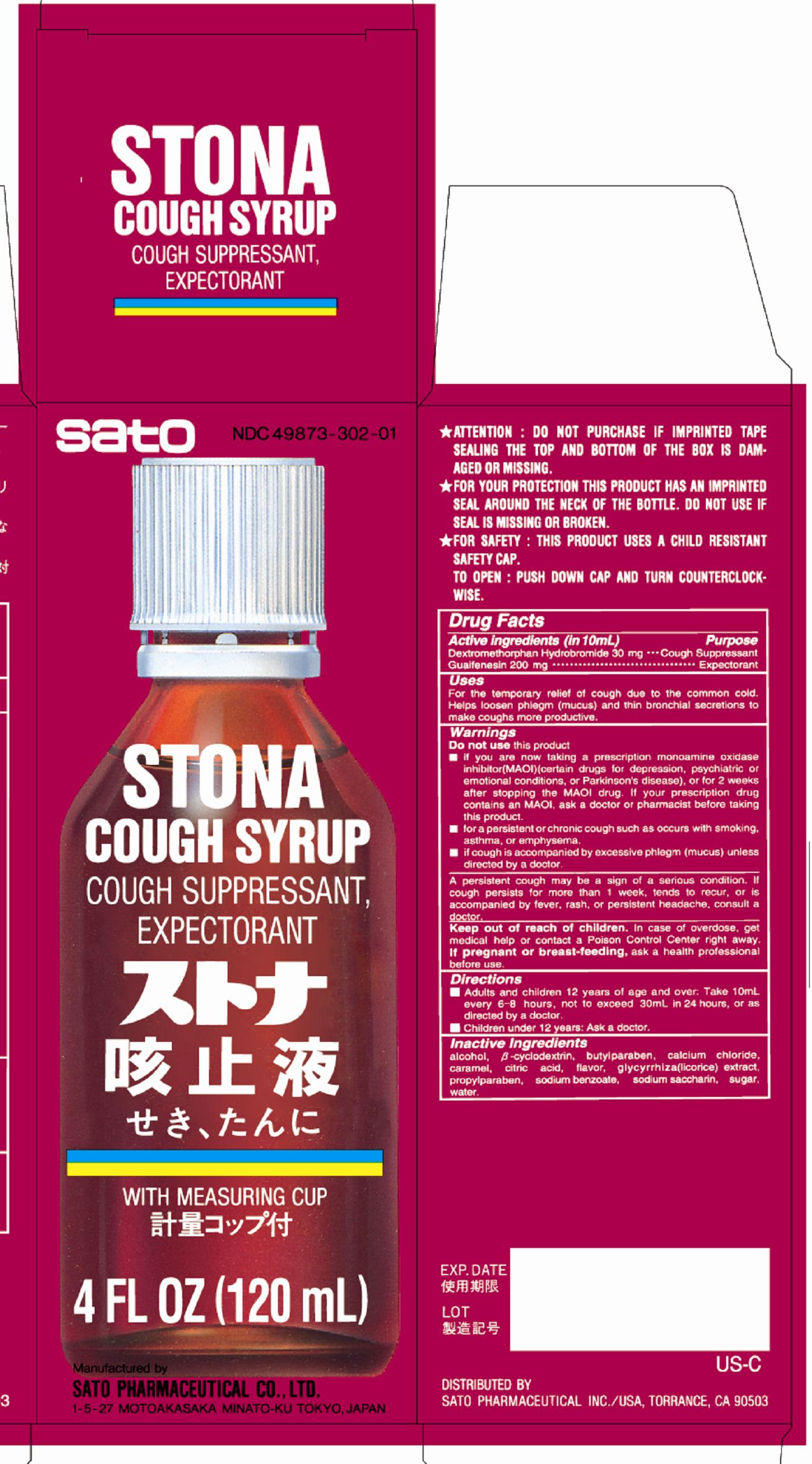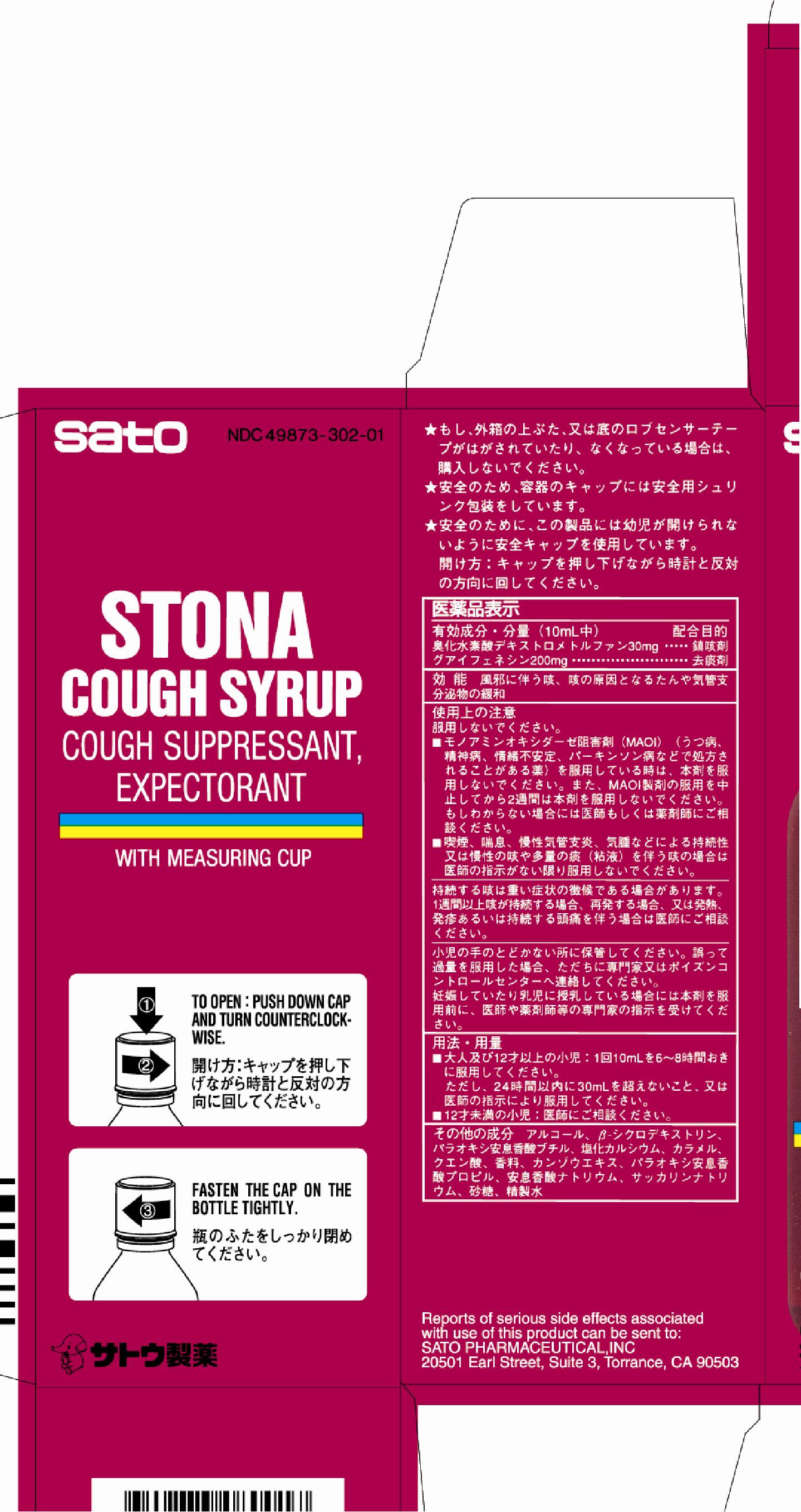 DRUG LABEL: Stona Cough
NDC: 49873-302 | Form: SYRUP
Manufacturer: Sato Pharmaceutical Co., Ltd.
Category: otc | Type: HUMAN OTC DRUG LABEL
Date: 20231112

ACTIVE INGREDIENTS: DEXTROMETHORPHAN HYDROBROMIDE 30 mg/10 mL; GUAIFENESIN 200 mg/10 mL
INACTIVE INGREDIENTS: ALCOHOL; BETADEX; BUTYLPARABEN; CALCIUM CHLORIDE; CARAMEL; CITRIC ACID MONOHYDRATE; GLYCYRRHIZA GLABRA; PROPYLPARABEN; SODIUM BENZOATE; SACCHARIN SODIUM; SUCROSE; WATER

Stona Cough Syrup

Active ingredients (in 10 mL)
Dextromethorphan hydrobromide 30 mg
Guaifenesin 200 mg

Purpose
Dextromethorphan hydrobromide Cough suppressant
Guaifenesin Expectorant

Uses
For the temporary relief of cough due to the common cold. Helps loosen phlegm (mucus) and thin bronchial secretions to make coughs more productive.

WARNINGS

Enter section text here

Do not use this product
■if you are now taking a prescription monoamine oxidase inhibitor (MAOI) (certain drugs for depression, psychiatric or emotional conditions, or Parkinson’s disease), or for 2 weeks after stopping the MAOI drug. If your prescription drug contains an MAOI, ask a doctor or pharmacist before taking this product.
■for a persistent or chronic cough such as occurs with smoking, asthma, or emphysema.
■if cough is accompanied by excessive phlegm (mucos) unless directed by a doctor.

PRECAUTIONS

A persistent cough may be a sign of a serious condition. If cough persists for more than 1 week, tends to recur, or is accompanied by fever, rash, or persistent headache, consult a doctor.

Keep out of reach of children. In case of accidental overdose, get medical help or contact a Poison Control Center right away.

PREGNANCY OR BREAST FEEDING

If pregnant or breast-feeding, ask a health professional before use.

Directions
■Adults and children 12 years of age and over: Take 10mL every 6 – 8 hours, not to exceed 30mL in 24 hours, or as directed by a doctor.
■Children under 12 years: Ask a doctor.

Inactive ingredients
alcohol, beta-cyclodextrin, butylparaben, calcium chloride, caramel, citric acid, flavor, glycyrrhiza (licorice) extract, propylparaben, sodium benzoate, sodium saccharin, sugar, water.

PACKAGE LABEL

stonacoughsyrcartA.jpg

PACKAGE LABEL

stonacoughsyrcartB.jpg